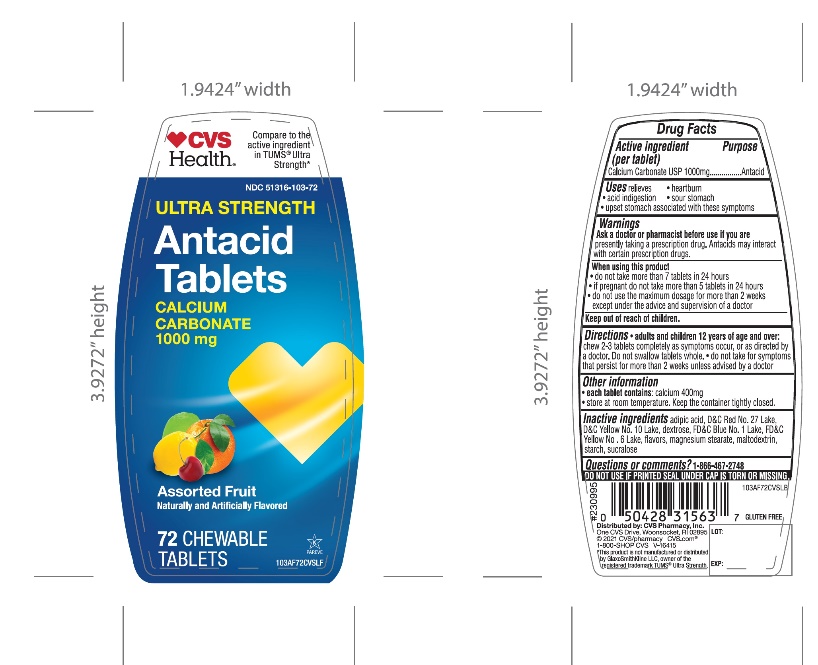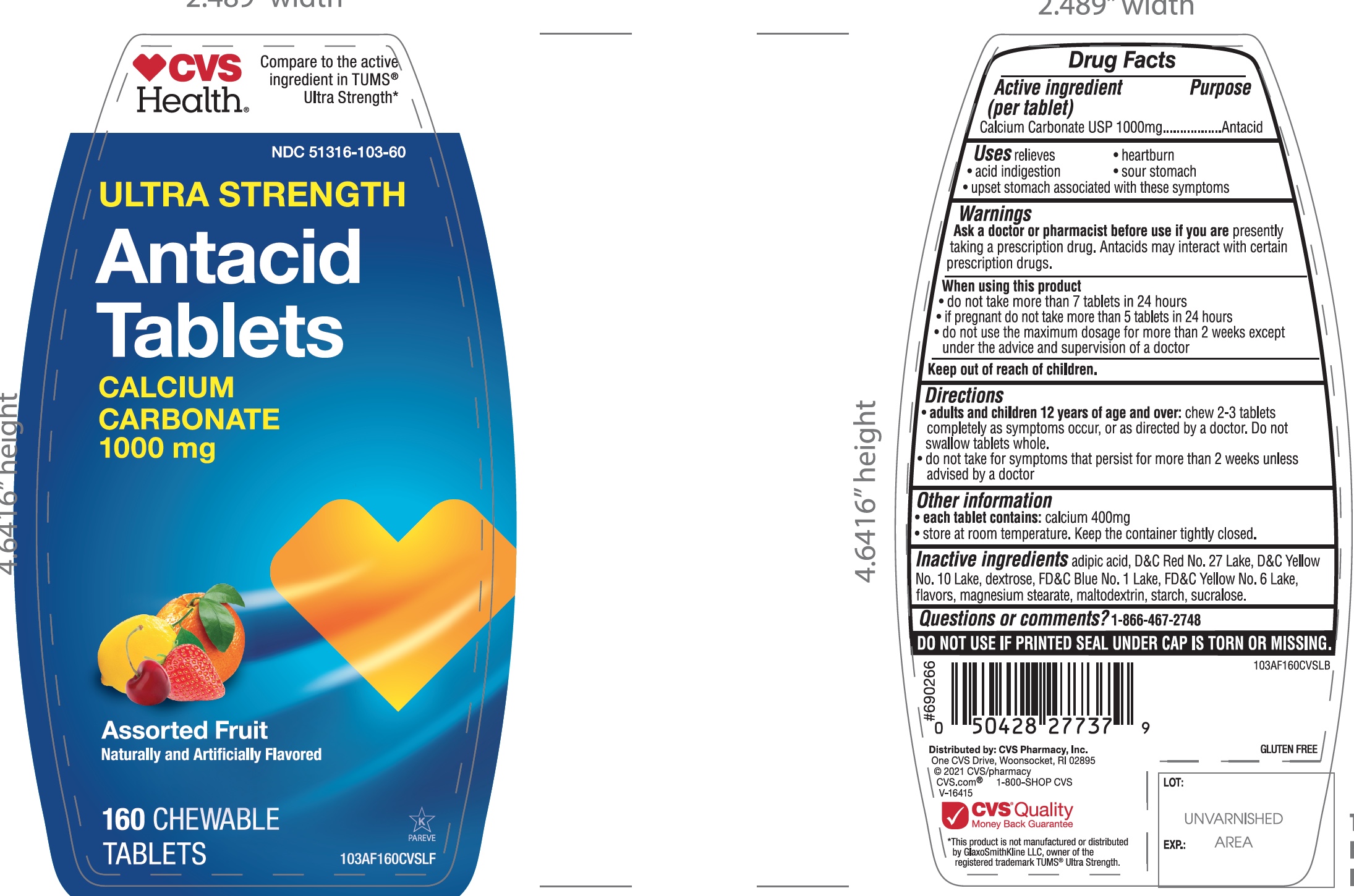 DRUG LABEL: CVS PHARMACY

NDC: 51316-103 | Form: TABLET, CHEWABLE
Manufacturer: CVS
Category: otc | Type: HUMAN OTC DRUG LABEL
Date: 20251204

ACTIVE INGREDIENTS: CALCIUM CARBONATE 1000 mg/1 1
INACTIVE INGREDIENTS: ADIPIC ACID; D&C RED NO. 27; D&C YELLOW NO. 10; DEXTROSE, UNSPECIFIED FORM; FD&C BLUE NO. 1; FD&C YELLOW NO. 6; MAGNESIUM STEARATE; MALTODEXTRIN; STARCH, CORN; SUCRALOSE

CVS Ultra Strength Antacid Assorted Fruit Calcium Carbonate 72 Chewable Tablets

Active ingredient (per tablet)

Calcium Carbonate USP 1000 mg

Purpose

Antacid

Uses

relieves

- heartburn
- acid indigestion
- sour stomach
- upset stomach associated with these symptoms

Warnings

Ask a doctor or pharmacist before use if you arepresently taking a prescription drug. Antacids may interact with certain prescription drugs.

When using this product

- do not take more than 7 tablets in 24 hours
- if pregnant do not take more than 5 tablets in 24 hours
- do not use the maximum dosage for more than 2 weeks except under the advice and supervision of a doctor.

Directions

- adults and children 12 years of age and over:chew 2-3 tablets completely as symptoms occur, or as directed by a doctor.
- do not take for symptoms that persist for more than 2 weeks unless advised by a doctor

Other information

- each tablet contains: calcium 400mg
- Store at room temperature. Keep the container tightly closed.

Inactive ingredients

adipic acid, D&C Red No. 27, D&C Yellow No. 10, dextrose, FD&C Blue No. 1, FD&C Yellow No. 6, flavors, magnesium stearate, maltodextrin, starch, sucralose.

Questions or comments?

1-866-467-2748

SAFETY SEALED: DO NOT USE IF PRINTED SEAL UNDER CAP IS TORN OR MISSING

Package/Label Principal Display Panel

NDC 51316-103-72

*Compare to the active ingredient in Ultra Strength Tums®

ULTRA STRENGTH

Antacid Tablets

Calcium Carbonate 1000 mg

Fast Relief of Upset Stomach, Heartburn, and Acid Indigestion

Assorted Fruit

Naturally and Artificially Flavored

72 Chewable Tablets

K PAREVE

GLUTEN- FREE

DISTRIBUTED BY

*This product is not manufactured or distributed by GlaxoSmithKline LLC, owner of the registered trademark Ultra Strength, Tums®

Package Label for 72 Chewable Tablets